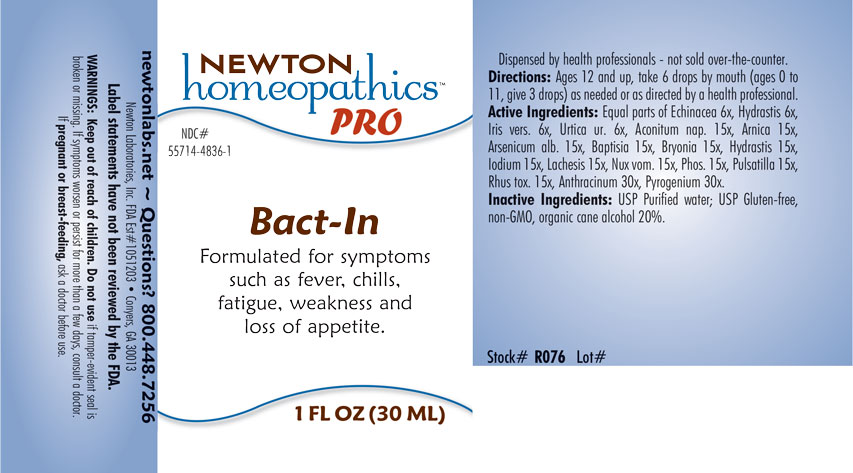 DRUG LABEL: Bact-In
NDC: 55714-4836 | Form: LIQUID
Manufacturer: Newton Laboratories, Inc.
Category: homeopathic | Type: HUMAN OTC DRUG LABEL
Date: 20201202

ACTIVE INGREDIENTS: ECHINACEA, UNSPECIFIED 6 [hp_X]/1 mL; RANCID BEEF 30 [hp_X]/1 mL; URTICA URENS 6 [hp_X]/1 mL; ACONITUM NAPELLUS 15 [hp_X]/1 mL; ARNICA MONTANA 15 [hp_X]/1 mL; ARSENIC TRIOXIDE 15 [hp_X]/1 mL; BAPTISIA TINCTORIA ROOT 15 [hp_X]/1 mL; BRYONIA ALBA ROOT 15 [hp_X]/1 mL; GOLDENSEAL 15 [hp_X]/1 mL; IODINE 15 [hp_X]/1 mL; LACHESIS MUTA VENOM 15 [hp_X]/1 mL; STRYCHNOS NUX-VOMICA SEED 15 [hp_X]/1 mL; PHOSPHORUS 15 [hp_X]/1 mL; ANEMONE PULSATILLA 15 [hp_X]/1 mL; TOXICODENDRON PUBESCENS LEAF 15 [hp_X]/1 mL; BACILLUS ANTHRACIS IMMUNOSERUM RABBIT 30 [hp_X]/1 mL; IRIS VERSICOLOR ROOT 6 [hp_X]/1 mL
INACTIVE INGREDIENTS: WATER; ALCOHOL

Bact-In 4836L

INDICATIONS & USAGE SECTION

Formulated for symptoms such as fever, chills, fatigue, weakness and loss of appetite.

DOSAGE & ADMINISTRATION SECTION

Directions: Ages 12 and up, take 6 drops by mouth (ages 0 to 11, give 3 drops) as needed or as directed by a health professional.

OTC - ACTIVE INGREDIENT SECTION

Equal parts of Echinacea 6x, Hydrastis canadensis 6x, Iris versicolor 6x, Urtica urens 6x, Aconitum napellus 15x, Arnica montana 15x, Arsenicum album 15x, Baptisia tinctoria 15x, Bryonia 15x, Hydrastis canadensis 15x, Iodium 15x, Lachesis mutus 15x, Nux vomica 15x, Phosphorus 15x, Pulsatilla 15x, Rhus toxicodendron 15x, Anthracinum 30x, Pyrogenium 30x.

OTC - PURPOSE SECTION

Formulated for symptoms such as fever, chills, fatigue, weakness and loss of appetite.

INACTIVE INGREDIENT SECTION

Inactive Ingredients: USP Purified Water; USP Gluten-free, non-GMO, organic cane alcohol 20%.

QUESTIONS SECTION

newtonlabs.net - Questions? 800.448.7256

Newton Laboratories, Inc. FDA Est # 1051203 Conyers, GA 30013

WARNINGS SECTION

WARNINGS: Keep out of reach of children. Do not use if tamper-evident seal is broken or missing. If symptoms worsen or persist for more than a few days, consult a doctor. If pregnant or breast-feeding, ask a doctor before use.

OTC - PREGNANCY OR BREAST FEEDING SECTION

If pregnant or breast-feeding, ask a doctor before use.

OTC - KEEP OUT OF REACH OF CHILDREN SECTION

Keep out of reach of children.